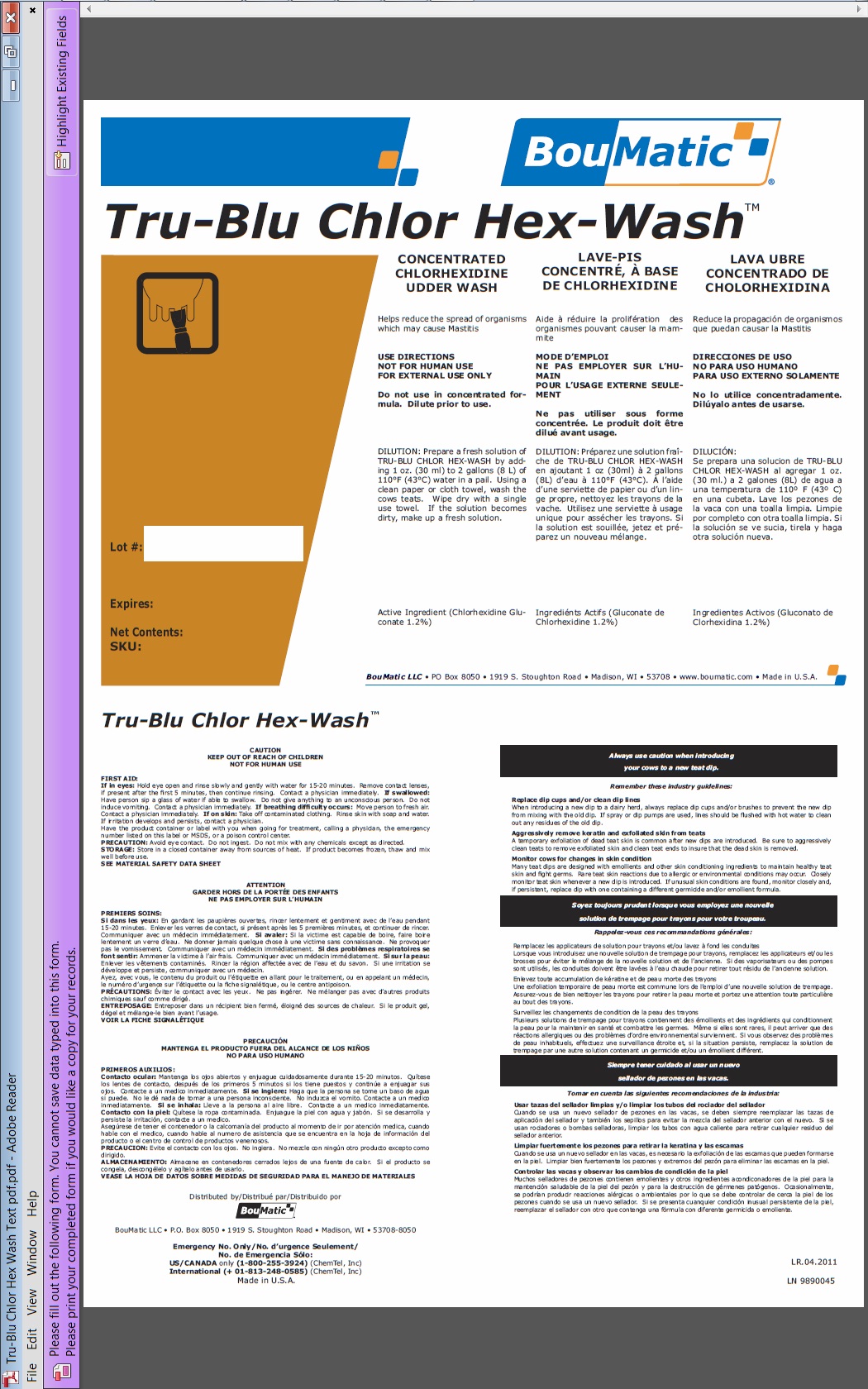 DRUG LABEL: Tru-Blu Chlor Hex-Wash
NDC: 48106-1114 | Form: LIQUID
Manufacturer: BouMatic, LLC
Category: animal | Type: OTC ANIMAL DRUG LABEL
Date: 20120101

ACTIVE INGREDIENTS: CHLORHEXIDINE GLUCONATE 132 mL/10 L

Tru-Blu Chlor Hex-Wash

INDICATIONS AND USAGE

CONCENTRATED CHLORHEXIDINE UDDER WASH
Helps reduce the spread of organisms which may cause Mastitis
USE DIRECTIONS
NOT FOR HUMAN USE
FOR EXTERNAL USE ONLY
Do not use in concentrated formula. Dilute prior to use.
DILUTION: Prepare a fresh solution of TRU-BLU CHLOR HEX-WASH by adding 1 oz. (30 ml) to 2 gallons (8 L) of 110°F (43°C) water in a pail. Using a clean paper or cloth towel, wash the cows teats. Wipe dry with a single use towel. If the solution becomes dirty, make up a fresh solution.
Active Ingredient (Chlorhexidine Gluconate 1.2%)
Emollients (Glycerin 5%)

PRECAUTIONS

CAUTION
KEEP OUT OF REACH OF CHILDREN
NOT FOR HUMAN USE
FIRST AID:
If in eyes: Hold eye open and rinse slowly and gently with water for 15-20 minutes. Remove contact lenses,
if present after the first 5 minutes, then continue rinsing. Contact a physician immediately. If swallowed:
Have person sip a glass of water if able to swallow. Do not give anything to an unconscious person. Do not
induce vomiting. Contact a physician immediately. If breathing difficulty occurs: Move person to fresh air.
Contact a physician immediately. If on skin: Take off contaminated clothing. Rinse skin with soap and water.
If irritation develops and persists, contact a physician.
Have the product container or label with you when going for treatment, calling a physician, the emergency
number listed on this label or MSDS, or a poison control center.
PRECAUTION: Avoid eye contact. Do not ingest. Do not mix with any chemicals except as directed.
STORAGE: Store in a closed container away from sources of heat. If product becomes frozen, thaw and mix
well before use.
SEE MATERIAL SAFETY DATA SHEET